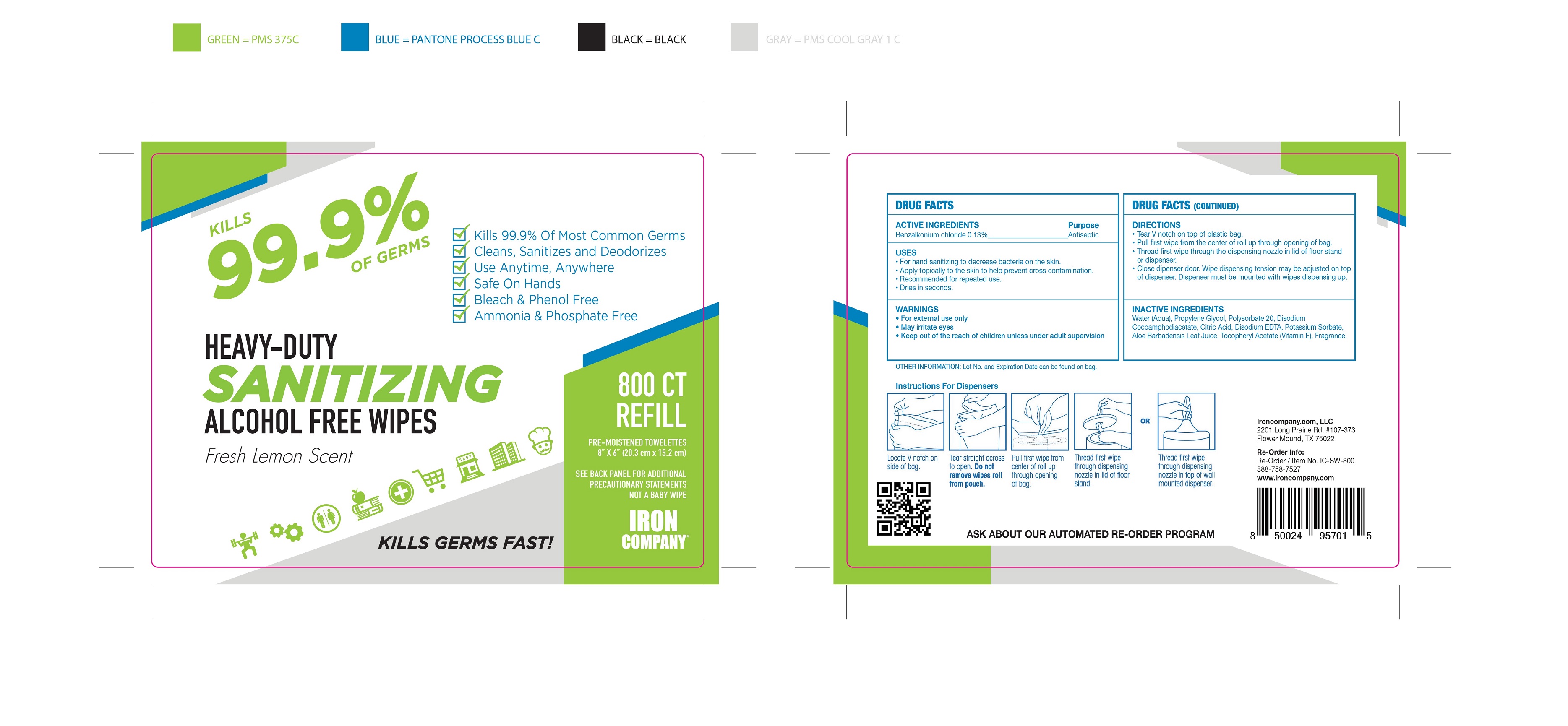 DRUG LABEL: SANITIZING ALCOHOL FREE WIPES
NDC: 81244-001 | Form: CLOTH
Manufacturer: Ironcompany.com, LLC
Category: otc | Type: HUMAN OTC DRUG LABEL
Date: 20231024

ACTIVE INGREDIENTS: BENZALKONIUM CHLORIDE 0.13 g/100 g
INACTIVE INGREDIENTS: WATER; PROPYLENE GLYCOL; POLYSORBATE 20; DISODIUM COCOAMPHODIACETATE; CITRIC ACID MONOHYDRATE; EDETATE DISODIUM ANHYDROUS; POTASSIUM SORBATE; .ALPHA.-TOCOPHEROL ACETATE; FRAGRANCE LEMON ORC2001060; ALOE VERA LEAF

81244-001 SANITIZING ALCOHOL FREE WIPES

ACTIVE INGREDIENTS

Benzalkonium chloride 0.13%

Purpose

Antiseptic

USES

For hand sanitizing to decrease bacteria on the skin.

Apply topically to the skin to help prevent cross contamination.

Recommended for repeated use.

Dries in seconds.

WARNINGS

For external use only

May irritate eyes

Keep out of the reach of children unless under adult supervision

KEEP OUT OF REACH OF CHILDREN

Keep out of the reach of children unless under adult supervision

DIRECTIONS

Tear V notch on top of plastic bag.

Pull first wipe from the center of roll up through opening of bag.

Thread first wipe through the dispensing nozzle in lid of floor stand or dispenser.

Close dipenser door. Wipe dispensing tension may be adjusted on top of dispenser. Dispenser must be mounted with wipes dispensing up.

INACTIVE INGREDIENTS

Water (Aqua), Propylene Glycol, Polysorbate 20, Disodium Cocoamphodiacetate, Citric Acid, Disodium EDTA, Potassium Sorbate, Aloe Barbadensis Leaf Juice, Tocopheryl Acetate (Vitamin E), Fragrance.

PACKAGE LABEL

800 CT REFILL, NDC: 81244-001-01